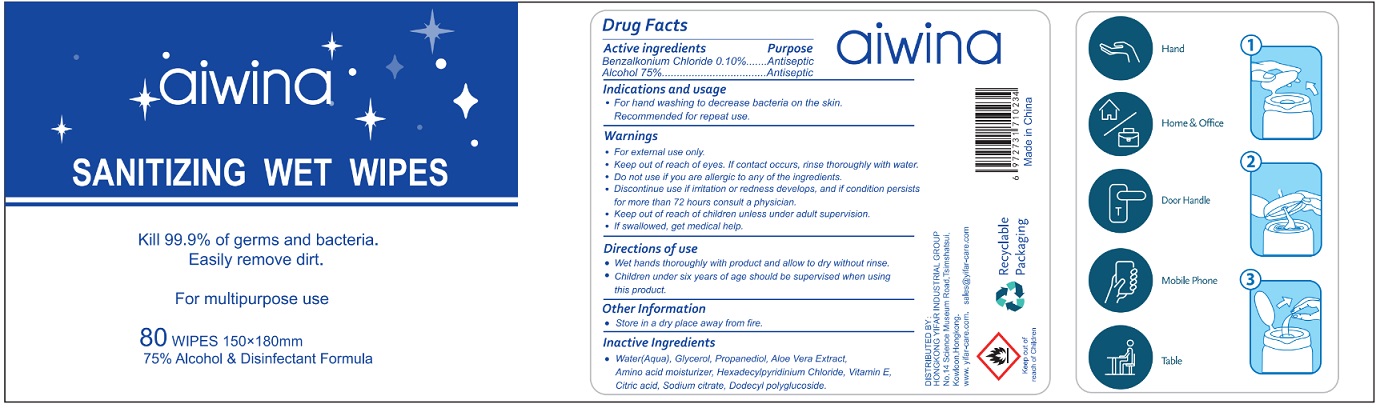 DRUG LABEL: AIWINA Sanitizing Wet Wipes
NDC: 79011-001 | Form: CLOTH
Manufacturer: HONGKONG YIFAR INDUSTRIAL LIMITED
Category: otc | Type: HUMAN OTC DRUG LABEL
Date: 20200617

ACTIVE INGREDIENTS: ALCOHOL 75 mL/100 mL; BENZALKONIUM CHLORIDE 0.1 g/100 mL
INACTIVE INGREDIENTS: WATER; GLYCERIN; PROPANEDIOL; ALOE VERA LEAF; BETAINE; CETYLPYRIDINIUM CHLORIDE; ALPHA-TOCOPHEROL; CITRIC ACID MONOHYDRATE; SODIUM CITRATE; LAURYL GLUCOSIDE

Active Ingredients

Benzalkonium Chloride 0. 10%

Alcohol 75%

Purpose

Antiseptic, Hand Sanitizer

Uses

- For hand washing to decrease bacteria on the skin.
- Recommended for repeat use.

Warnings

For external use only.
Keep out of reach of eyes. If contact occurs, rinse thoroughly with water.
Do not use if you are allergic to any of the ingredients.
Discontinue use if irritation or redness develops, and if condition persists for more than 72 hours consult a physician.

• Keep out of reach of children unless under adult supervision.
• If swallowed, get medical help.

Directions of use

- Wet hands thoroughly with product and allow to dry without rinse.
- Children under six years of age should be supervised when using this product.

Other information

Store in a dry place away from fire.

Inactive ingredients

Water(Aqua), Glycerol, Propanediol, Aloe Vera Extract, Amino acid moisturizer, Hexadecylpyridinium Chloride, Vitamin E, Citric acid, Sodium citrate, Dodecyl polyglucoside.